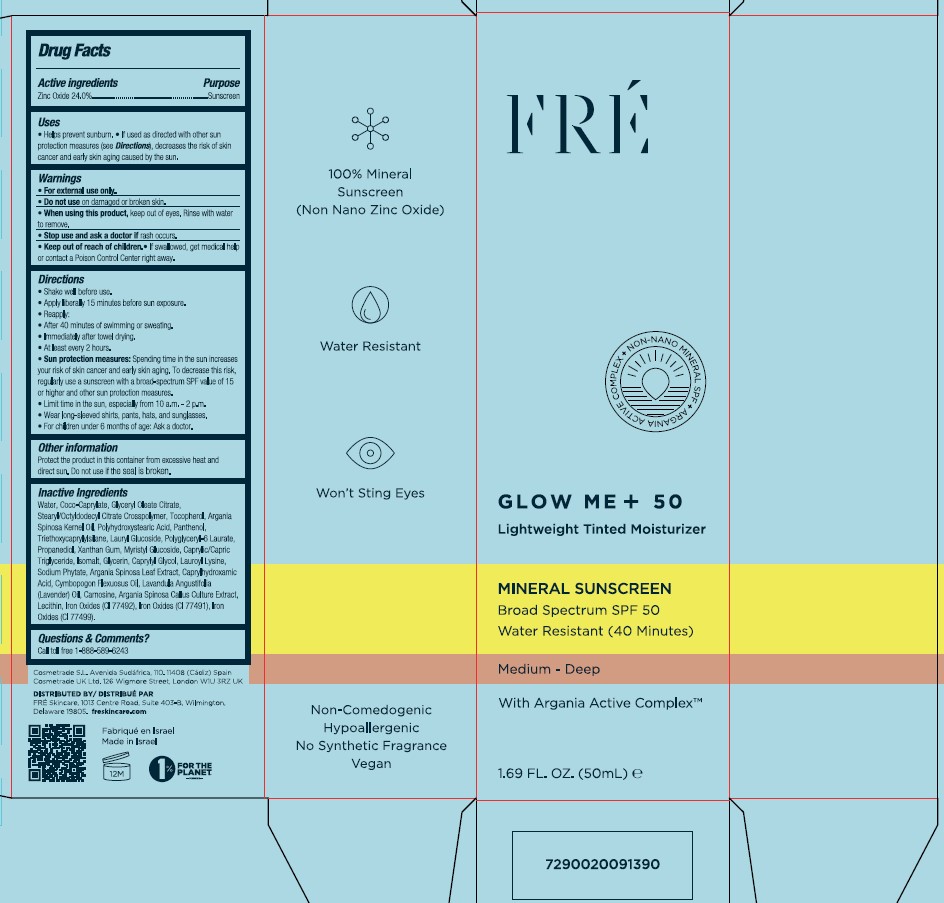 DRUG LABEL: FRE GLOW ME SPF 50 Lightweight Tinted Moisturizer Medium Deep
NDC: 69435-1408 | Form: CREAM
Manufacturer: Peer Pharm Ltd
Category: otc | Type: HUMAN OTC DRUG LABEL
Date: 20260112

ACTIVE INGREDIENTS: ZINC OXIDE 24 g/100 mL
INACTIVE INGREDIENTS: EAST INDIAN LEMONGRASS OIL; LECITHIN, SOYBEAN; FERRIC OXIDE YELLOW; FERRIC OXIDE RED; ARGANIA SPINOSA LEAF; CAPRYLHYDROXAMIC ACID; MYRISTYL GLUCOSIDE; PANTHENOL; COCO-CAPRYLATE; STEARYL/OCTYLDODECYL CITRATE CROSSPOLYMER; TOCOPHEROL; POLYHYDROXYSTEARIC ACID (2300 MW); POLYGLYCERYL-6 LAURATE; FERROSOFERRIC OXIDE; LAVENDER OIL; LAURYL GLUCOSIDE; ARGAN OIL; GLYCERIN; CAPRYLYL GLYCOL; XANTHAN GUM; PROPANEDIOL; MEDIUM-CHAIN TRIGLYCERIDES; PHYTATE SODIUM; CARNOSINE; ARGANIA SPINOSA WHOLE; LAUROYL LYSINE; WATER; TRIETHOXYCAPRYLYLSILANE; ISOMALT; GLYCERYL MONOOLEATE CITRATE

FRE GLOW ME SPF 50 Lightweight Tinted Moisturizer Medium-Deep

Active ingredients

Zinc Oxide 24.0%

Purpose

Sunscreen

Uses

• Helps prevent sunburn.

• If used as directed with other sun protection measures (see Directions), decreases the risk of skin
cancer and early skin aging caused by the sun.

Warnings

For external use only.

Do not use

on damaged or broken skin.

When using this product

keep out of eyes. Rinse with water to remove.

Stop use and ask a doctor

if rash occurs.

Keep out of reach of children

If swallowed, get medical help or contact a Poison Control Center right away.

Directions

• Shake well before use.
• Apply liberally 15 minutes before sun exposure.
• Reapply:
• After 40 minutes of swimming or sweating.
• Immediately after towel drying.
• At least every 2 hours.
• Sun protection measures: Spending time in the sun increases
your risk of skin cancer and early skin aging. To decrease this risk,
regularly use a sunscreen with a broad-spectrum SPF value of 15
or higher and other sun protection measures.
• Limit time in the sun, especially from 10 a.m. - 2 p.m.
• Wear long-sleeved shirts, pants, hats, and sunglasses.
• For children under 6 months of age: Ask a doctor.

Other information

Protect the product in this container from excessive heat and
direct sun. Do not use if the seal is broken.

Inactive Ingredients

Water, Coco-Caprylate, Glyceryl Oleate Citrate,
Stearyl/Octyldodecyl Citrate Crosspolymer, Tocopherol, Argania
Spinosa Kernel Oil, Polyhydroxystearic Acid, Panthenol,
Triethoxycaprylylsilane, Lauryl Glucoside, Polyglyceryl-6 Laurate,
Propanediol, Xanthan Gum, Myristyl Glucoside, Caprylic/Capric
Triglyceride, Isomalt, Glycerin, Caprylyl Glycol, Lauroyl Lysine,
Sodium Phytate, Argania Spinosa Leaf Extract, Caprylhydroxamic
Acid, Cymbopogon Flexuosus Oil, Lavandula Angustifolia
(Lavender) Oil, Carnosine, Argania Spinosa Callus Culture Extract,
Lecithin, Iron Oxides (CI 77492), Iron Oxides (CI 77491), Iron
Oxides (CI 77499).

Questions and Comments

Call toll free 1-888-589-6243